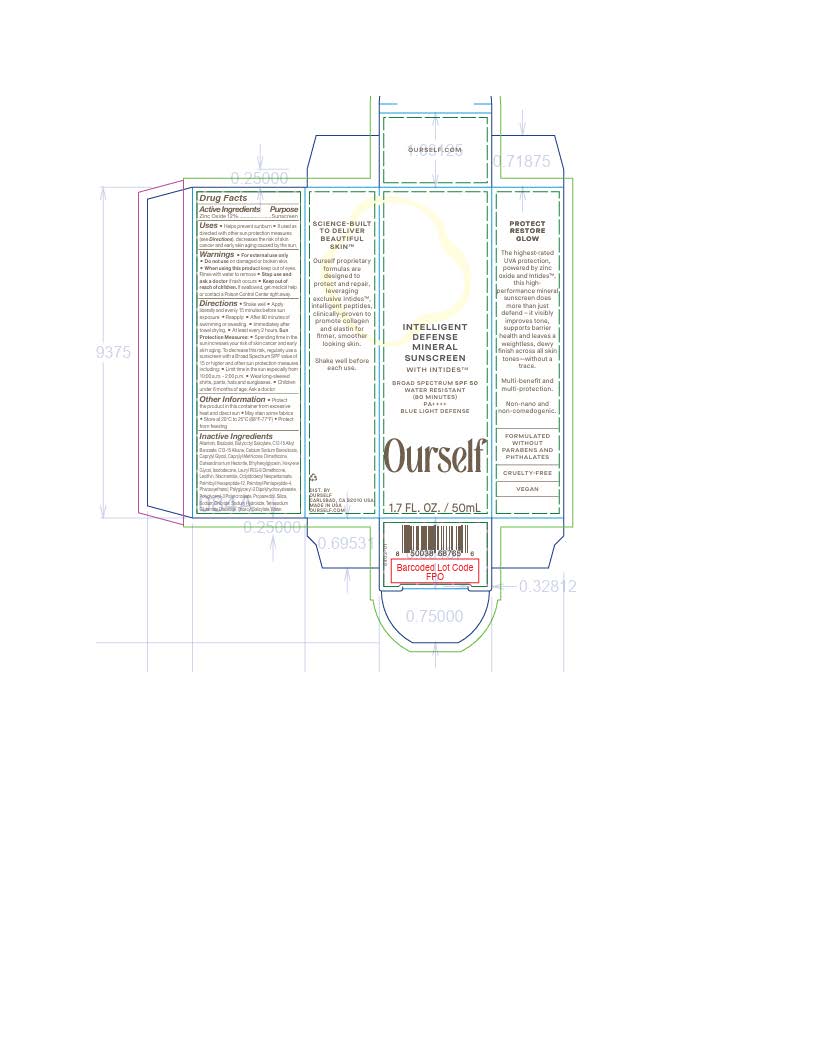 DRUG LABEL: Intelligent Defense Mineral Sunscreen
NDC: 82325-2588 | Form: LOTION
Manufacturer: GLO PHARMA
Category: otc | Type: HUMAN OTC DRUG LABEL
Date: 20260212

ACTIVE INGREDIENTS: ZINC OXIDE 12 mg/1 mL
INACTIVE INGREDIENTS: TOCOPHEROL; ROSMARINUS OFFICINALIS WHOLE; METHYLHEPTYL ISOSTEARATE; NYLON-12; PHENYLPROPANOL; ALKYL (C12-15) BENZOATE; PROPANEDIOL; WATER; CAPRYLYL GLYCOL; TRIDECYL SALICYLATE; ALLANTOIN; SODIUM CHLORIDE; LECITHIN, SOYBEAN; SILICON DIOXIDE; POLYGLYCERYL-2 DIPOLYHYDROXYSTEARATE; TETRASODIUM GLUTAMATE DIACETATE; HELIANTHUS ANNUUS FLOWERING TOP; PALMITOYL PENTAPEPTIDE-4; SODIUM HYDROXIDE; PALMITOYL HEXAPEPTIDE-12; ORYZA SATIVA WHOLE; COCO-CAPRYLATE; .BETA.-BISABOLOL; NIACINAMIDE; METHYLPROPANEDIOL

Intelligent Defense Mineral Sunscreen